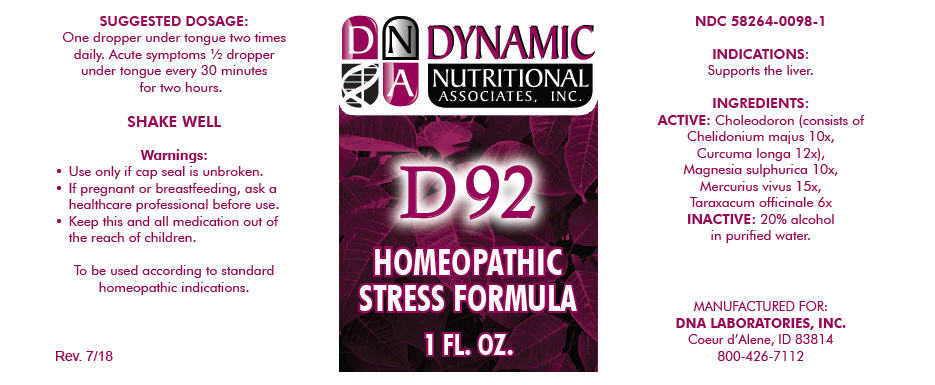 DRUG LABEL: D-92
NDC: 58264-0098 | Form: SOLUTION
Manufacturer: DNA Labs, Inc.
Category: homeopathic | Type: HUMAN OTC DRUG LABEL
Date: 20250113

ACTIVE INGREDIENTS: CHELIDONIUM MAJUS 10 [hp_X]/1 mL; TURMERIC 12 [hp_X]/1 mL; MAGNESIUM SULFATE HEPTAHYDRATE 10 [hp_X]/1 mL; MERCURY 15 [hp_X]/1 mL; TARAXACUM OFFICINALE 6 [hp_X]/1 mL
INACTIVE INGREDIENTS: ALCOHOL; WATER

D-92

NDC 58264-0098-1

INDICATIONS

PURPOSE

Supports the liver.

INGREDIENTS

ACTIVE

Choleodoron (consists of Chelidonium majus 10x, Curcuma longa 12x), Magnesia sulphurica 10x, Mercurius vivus 15x, Taraxacum officinale 6x

INACTIVE

20% alcohol in purified water.

SUGGESTED DOSAGE

One dropper under tongue two times daily. Acute symptoms ½ dropper under tongue every 30 minutes for two hours.

STORAGE AND HANDLING

SHAKE WELL

Warnings

- Use only if cap seal is unbroken.

PREGNANCY OR BREAST FEEDING

- If pregnant or breastfeeding, ask a healthcare professional before use.

KEEP OUT OF REACH OF CHILDREN

- Keep this and all medication out of the reach of children.

To be used according to standard homeopathic indications.

PRINCIPAL DISPLAY PANEL - 1 FL. OZ. Bottle Label

DYNAMIC
NUTRITIONAL
ASSOCIATES, INC.

D 92

HOMEOPATHIC
STRESS FORMULA

1 FL. OZ.